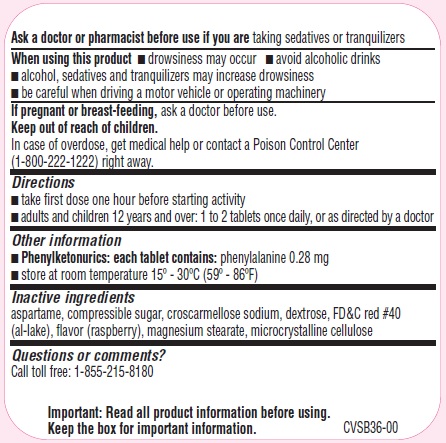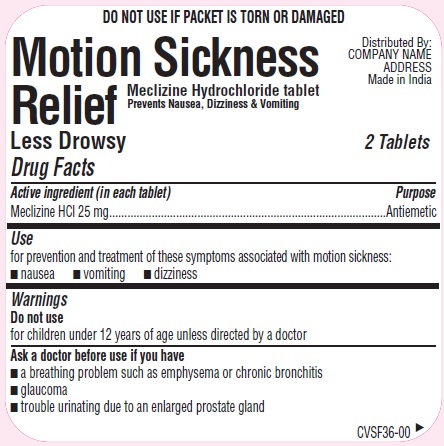 DRUG LABEL: Motion Sickness Relief
NDC: 51013-322 | Form: TABLET, CHEWABLE
Manufacturer: PuraCap Pharmaceutical LLC
Category: otc | Type: HUMAN OTC DRUG LABEL
Date: 20171128

ACTIVE INGREDIENTS: MECLIZINE HYDROCHLORIDE 25 mg/1 1
INACTIVE INGREDIENTS: ASPARTAME; CROSCARMELLOSE SODIUM; DEXTROSE; FD&C RED NO. 40; RASPBERRY; MAGNESIUM STEARATE; MICROCRYSTALLINE CELLULOSE; SUCROSE

Motion Sickness Relief

Active ingredient (in each tablet)

Meclizine Hydrochloride 25 mg

Purpose

Antiemetic

Uses

for prevention and treatment of these symptoms associated with motion sickness:

- nausea
- vomiting
- dizziness

Warnings

Do not use

for children under 12 years of age unless directed by a doctor

Ask a doctor before use if you have

- a breathing problem such as emphysema or chronic bronchitis
- glaucoma
- trouble urinating due to an enlarged prostate gland

Ask a doctor or pharmacist before use if you are

taking sedatives or tranquilizers

When using this product

- drowsiness may occur
- avoid alcoholic drinks
- alcohol, sedatives, and tranquilizers may increase drowsiness
- be careful when driving a motor vehicle or operating machinery

If pregnant or breast-feeding,

ask a doctor before use.

Keep out of reach of children.

In case of overdose, get medical help or contact a Poison Control Center (1-800-222-1222) right away.

Directions

- take first dose one hour before starting activity
- adults and children 12 years and over: 1 to 2 tablets once daily, or as directed by a doctor

Other information

- Phenylketonurics: each tablet contains: phenylalanine 0.28 mg
- store at room temperature 15º - 30ºC (59º - 86ºF)

Inactive ingredients

Aspartame, compressible sugar, croscarmellose sodium, dextrose, FD&C red 40 (al-lake), magnesium stearate, microcrystalline cellulose, raspberry flavor

Questions or comments?

Call toll free: 1-855-215-8180

PRINCIPAL DISPLAY PANEL

Motion Sickness Relief

30 Tablets 15 Pouches (2 Tablets per Pouch)

NDC 51013-322-54